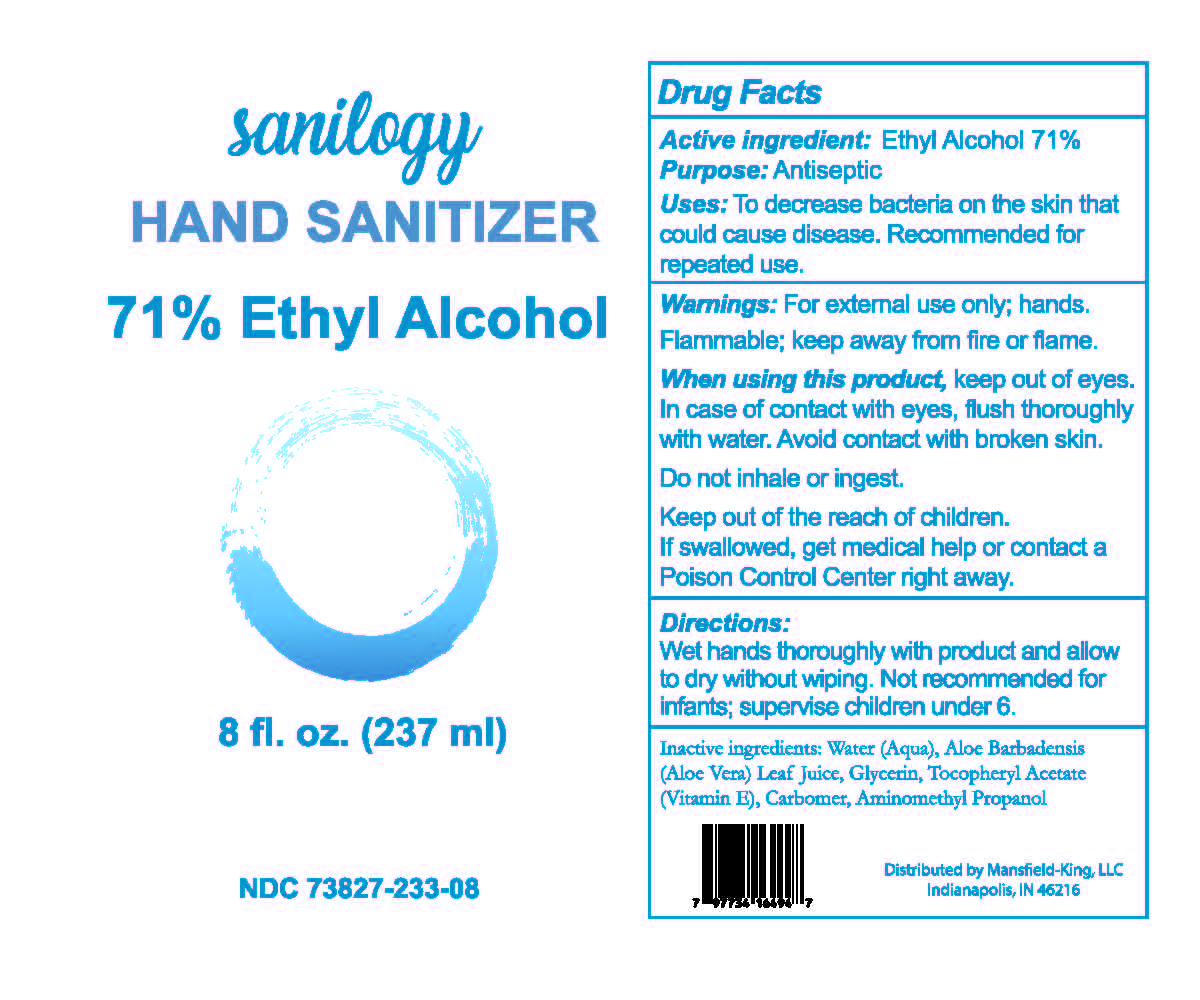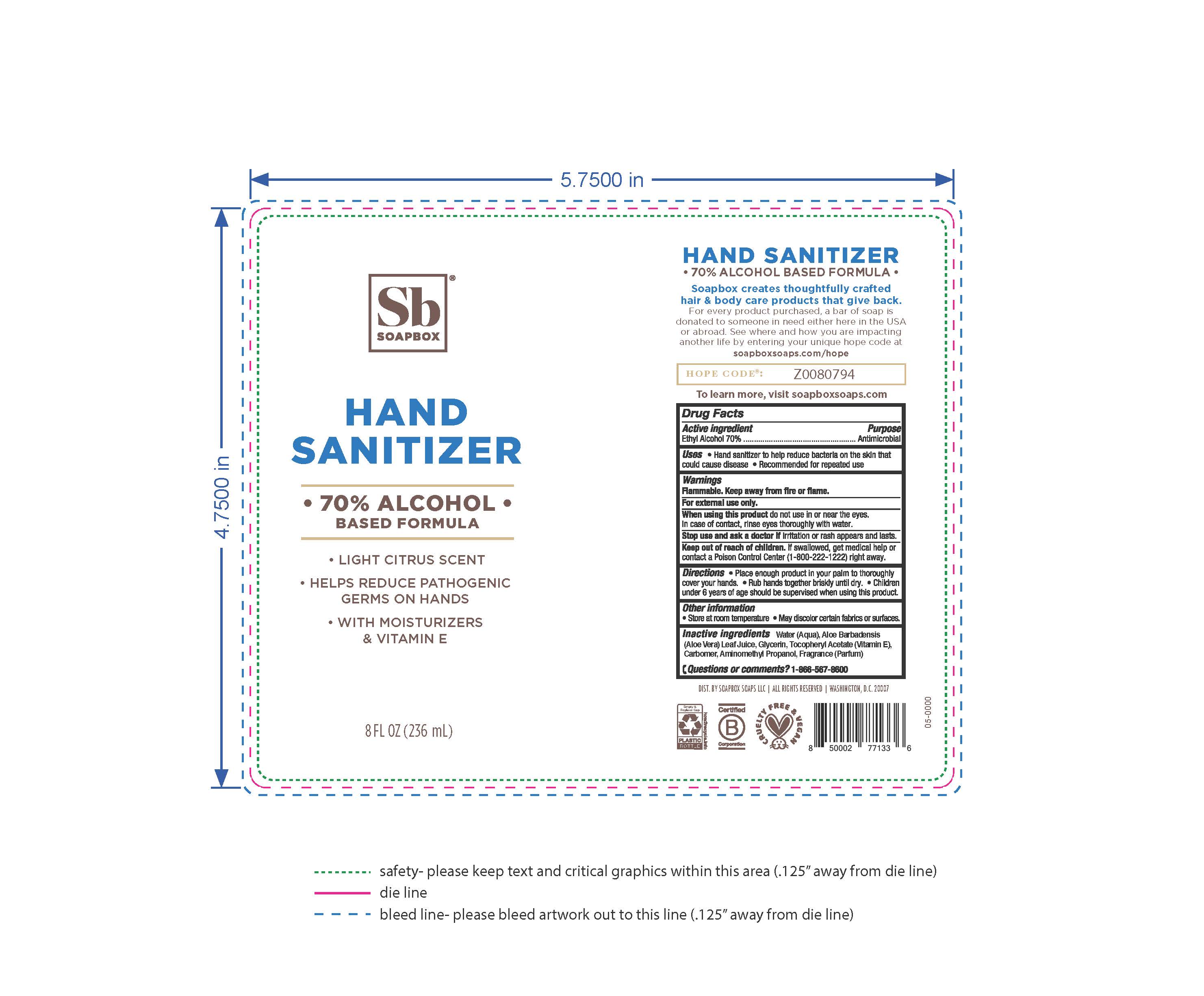 DRUG LABEL: Hand Sanitizer
NDC: 73827-233 | Form: GEL
Manufacturer: Mansfield-King, LLC
Category: otc | Type: HUMAN OTC DRUG LABEL
Date: 20201105

ACTIVE INGREDIENTS: ALCOHOL 75.769 mL/100 mL
INACTIVE INGREDIENTS: AMINOMETHYLPROPANOL 0.3155 mL/100 mL; ALOE VERA LEAF 1.684 mL/100 mL; ALPHA-TOCOPHEROL ACETATE 0.000026 mL/100 mL; WATER 21.5971 mL/100 mL; CARBOMER INTERPOLYMER TYPE A (55000 CPS) 0.3007 mL/100 mL; GLYCERIN 0.3341 mL/100 mL

Purpose

Antiseptic

Uses

To decrease bacteria on the skin that can cause disease. Recommended for repeated use.

Do not use

Do not inhale or ingest.

When using

When using this product, keep out of eyes. In case of contact with eyes, flush thoroughly with water. Avoid contact with broken skin. Do not inhale or ingest. If swallowed, get medical help or contact a Poison Control Center right away.

Keep out of the reach of children.

Directions.

Wet hands thoroughly with product and allow to dry without wiping.

STORAGE AND HANDLING

Flammable; keep away from fire or flame.

Inactive ingredients.

Water (Aqua), Aloe Barbadensis (Aloe Vera) Leaf Juice, Glycerin Tocopheryl Acetate (Vitamin E), Carbomer, Aminomethyl Propanol

Active Ingredient.

Ethyl Alcohol 71%

Warnings.

For external use only; hands. Flammable; keep away from fire or flame.